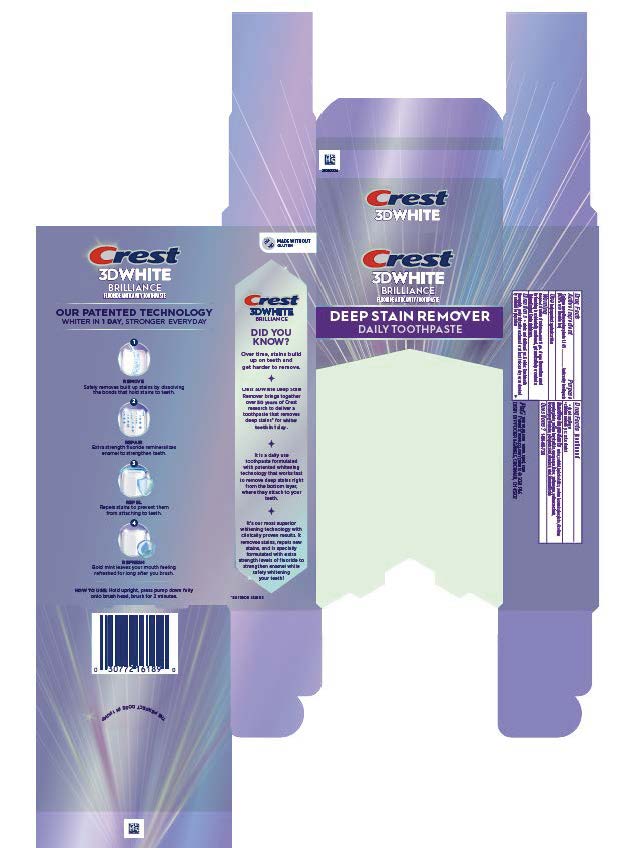 DRUG LABEL: Crest 3D White
NDC: 84126-611 | Form: PASTE, DENTIFRICE
Manufacturer: The Procter & Gamble Manufacturing Company
Category: otc | Type: HUMAN OTC DRUG LABEL
Date: 20260107

ACTIVE INGREDIENTS: SODIUM MONOFLUOROPHOSPHATE 2 mg/1 g
INACTIVE INGREDIENTS: HYDRATED SILICA; SACCHARIN SODIUM; COCAMIDOPROPYL BETAINE; TITANIUM DIOXIDE; MICA; SODIUM HEXAMETAPHOSPHATE; XANTHAN GUM; SODIUM LAURYL SULFATE; WATER; SUCRALOSE; SODIUM ACID PYROPHOSPHATE; CARRAGEENAN; PHOSPHORIC ACID; SORBITOL

Crest 3D White Deep Stain Remover Ultra White

Drug Facts

Sodium monofluorophosphate 1.14%

(0.20% w/v fluoride ion)

Purpose

Anticavity toothpaste

Use

helps protect against cavities

Warning

Keep out of reach of children under 6 yrs. of age. If more than used for brushing is accidentally swallowed, get medical help or contact Poison Control Center right away.

Directions

- adults and children 6 yrs. & older: Brush teeth
  thoroughly, preferably after each meal or at least twice a day, or as directed
  by a dentist or physician.
  • do not swallow
  • children under 6 yrs.: ask a dentist

Inactive ingredients

water, sorbitol, hydrated silica, sodium hexametaphosphate, disodium
pyrophosphate, sodium lauryl sulfate, carrageenan, flavor, xanthan gum, sodium saccharin,
cocamidopropyl betaine, phosphoric acid, sucralose, mica, titanium dioxide

Questions?

1-800-492-7378

DISTR. BY PROCTER & GAMBLE, CINCINNATI, OH 45202

Crest 3D White Brilliance 87g tube in carton

Crest

3D WHITE

BRILLIANCE

FLUORIDE ANTICAVITY TOOTHPASTE

DEEP STAIN REMOVER

DAILY TOOTHPASTE